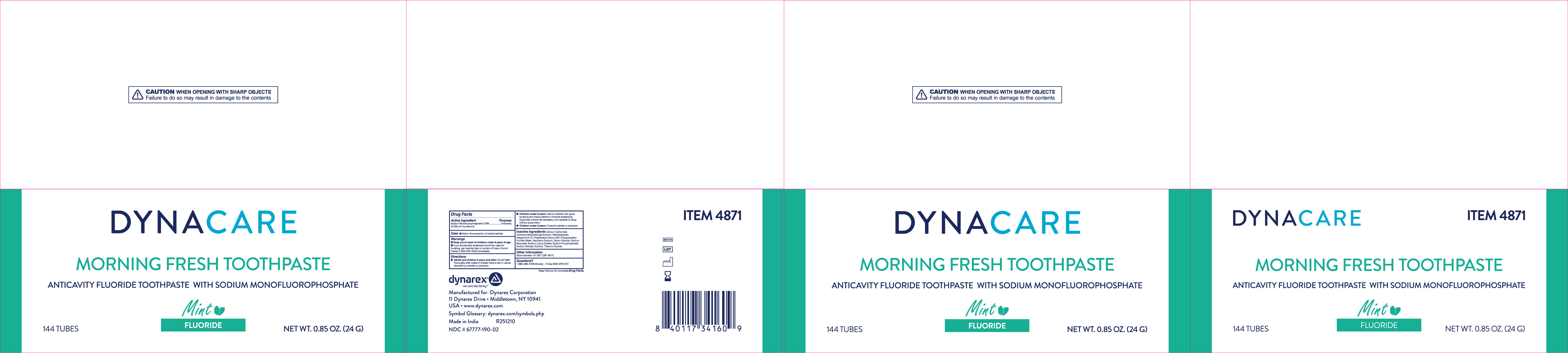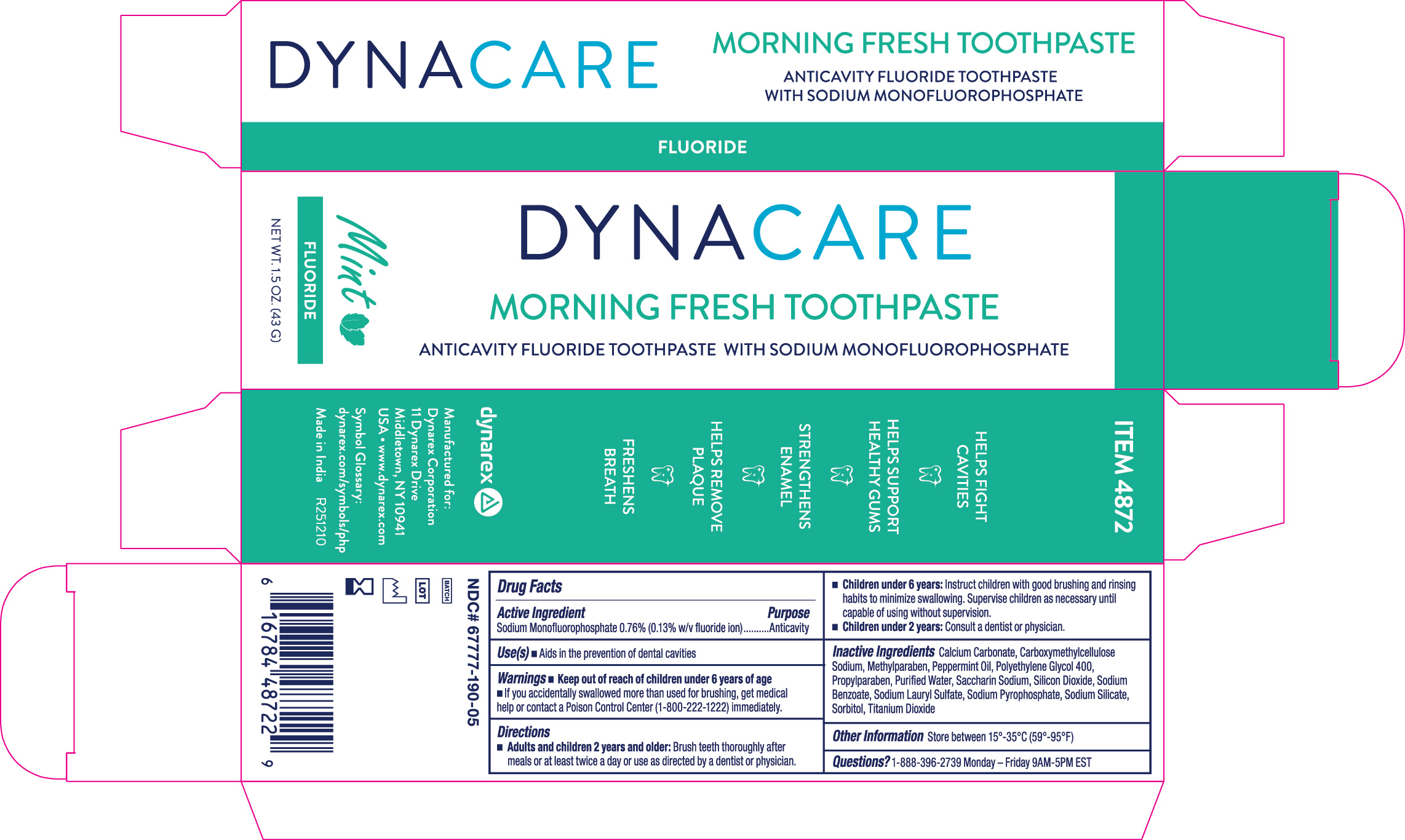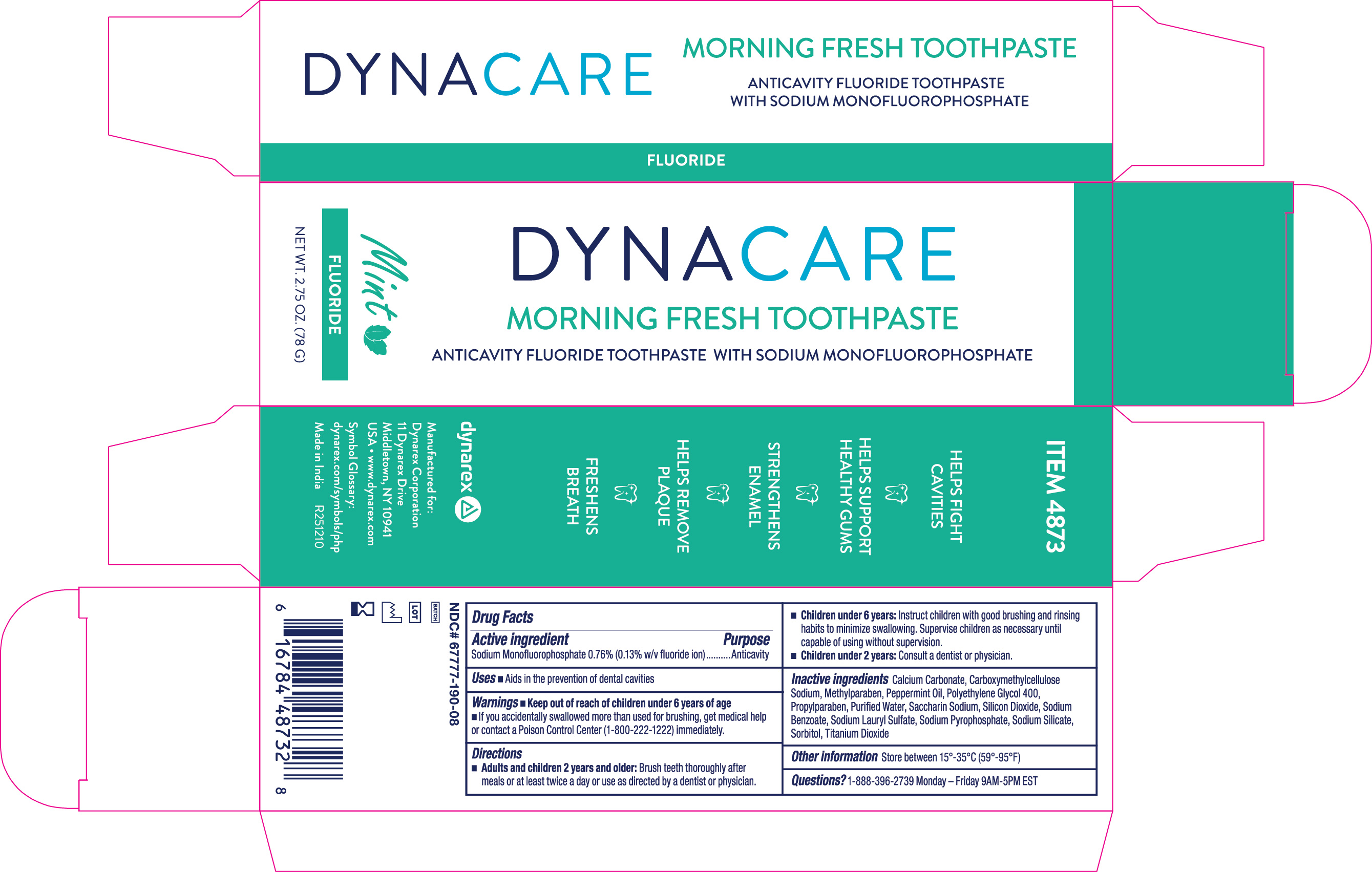 DRUG LABEL: Morning Fresh Mint Toothpaste, with Fluoride
NDC: 67777-190 | Form: PASTE
Manufacturer: Dynarex Corporation
Category: otc | Type: HUMAN OTC DRUG LABEL
Date: 20250925

ACTIVE INGREDIENTS: SODIUM MONOFLUOROPHOSPHATE 1.3 mg/1 mL
INACTIVE INGREDIENTS: SODIUM SILICATE; WATER; CALCIUM CARBONATE; SODIUM LAURYL SULFATE; METHYLPARABEN; PROPYLPARABEN; SODIUM BENZOATE; SACCHARIN SODIUM; SORBITOL; CARBOXYMETHYLCELLULOSE SODIUM, UNSPECIFIED; SILICON DIOXIDE; TITANIUM DIOXIDE; PEPPERMINT OIL; POLYETHYLENE GLYCOL 400; SODIUM PYROPHOSPHATE

4871 Morning Fresh Mint Toothpaste, with Fluoride NDC # 67777-190-02

Active Ingredient

Sodium Monofluorophosphate 0.76% (0.13% w/v fluoride ion)

Purpose

Anticavity

Use(s)

Helps protect against cavities

Warning

Do Not Swallow

Keep out of reach of children under 6 years of age

If you accidentally swallow more than used for brushing, get medical help or contact a Poison Control Center (1-800-222-1222) immediately.

Directions

• Adults and children 2 years and older: Brush teeth thoroughly after meals or at least twice a day or use as directed by a dentist or physician.

• Children under 6 years: to minimize swallowing, use a pea size amount and supervise brushing and rinsing until good habits are established.

• Children under 2 years: Use as directed by a dentist or physician.

Inactive Ingredients

Calcium Carbonate, Carboxymethylcellulose Sodium, Methylparaben, Peppermint Oil, Polyethylene Glycol 400, Propylparaben, Purified Water, Saccharin Sodium, Silicon Dioxide, Sodium Benzoate, Sodium Lauryl Sulfate, Sodium Pyrophosphate, Sodium Silicate, Sorbitol, Titanium Dioxide

Other Information

Store between 15º - 35ºC (59º - 95ºF)

Questions?

1-888-396-2739 Monday - Friday 9AM - 5PM EST

Label

4871 Label

Label

4872 Label

Label

4873 Label